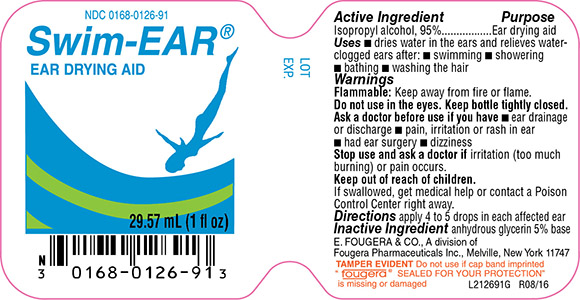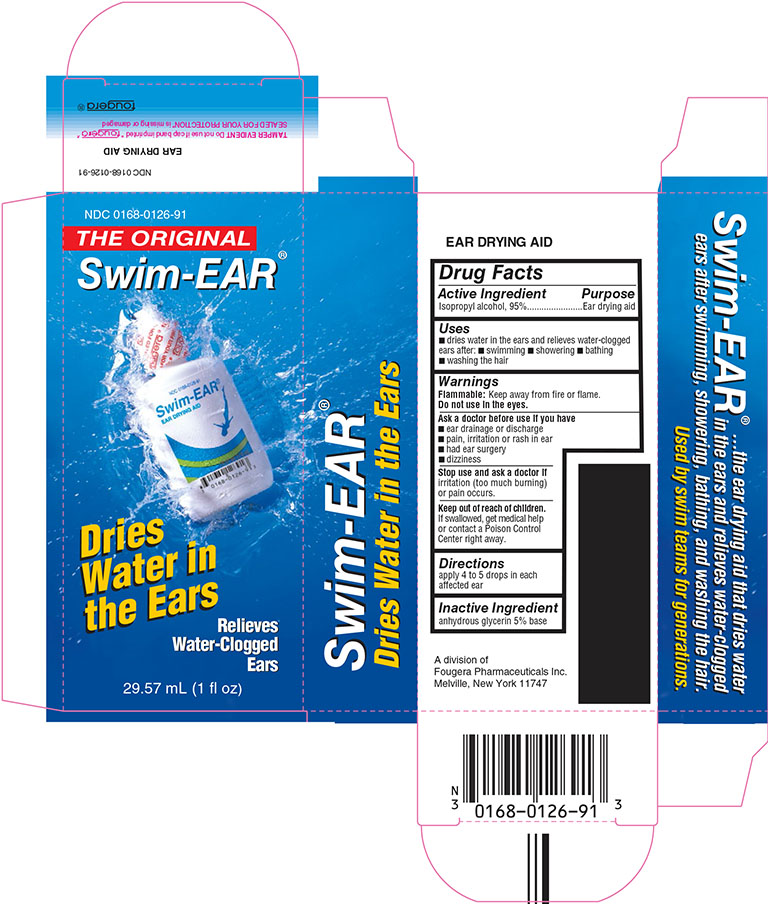 DRUG LABEL: Swim-EAR
NDC: 0168-0126 | Form: SOLUTION
Manufacturer: Fougera Pharmaceuticals Inc.
Category: otc | Type: HUMAN OTC DRUG LABEL
Date: 20210329

ACTIVE INGREDIENTS: ISOPROPYL ALCOHOL 950 mg/1 mL
INACTIVE INGREDIENTS: GLYCERIN

Swim-EAR ®
EAR DRYING AID

Active ingredient

Isopropyl alcohol, 95%

Purpose

Ear drying aid

Uses

Dries water in the ears and relieves water-clogged ears after:

- swimming
- showering
- bathing
- washing the hair.

Warnings

Flammable: Keep away from fire or flame.

Do not use in the eyes.

Ask a doctor before use if you have

- ear drainage or discharge
- pain, irritation or rash in ear
- had ear surgery
- dizziness

Stop use and ask a doctor if irritation (too much burning) or pain occurs.

Keep out of reach of children. If swallowed, get medical help or contact a Poison Control Center right away.

Directions
Apply 4 to 5 drops in each affected ear.

Inactive ingredient
Anhydrous glycerin 5% base.

E. FOUGERA & CO.
  A division of
  Fougera Pharmaceuticals Inc.
  Melville, New York 11747
  IP4808C
  R10/12
  #8

PACKAGE LABEL – PRINCIPAL DISPLAY PANEL – 1 Oz CONTAINER

NDC 0168-0126-91

Swim-EAR®

EAR DRYING AID

29.57 mL (1 fl oz)

PACKAGE LABEL – PRINCIPAL DISPLAY PANEL – 1 Oz Carton

NDC 0168-0126-91

Swim-EAR®

EAR DRYING AID

29.57 mL (1 fl oz)